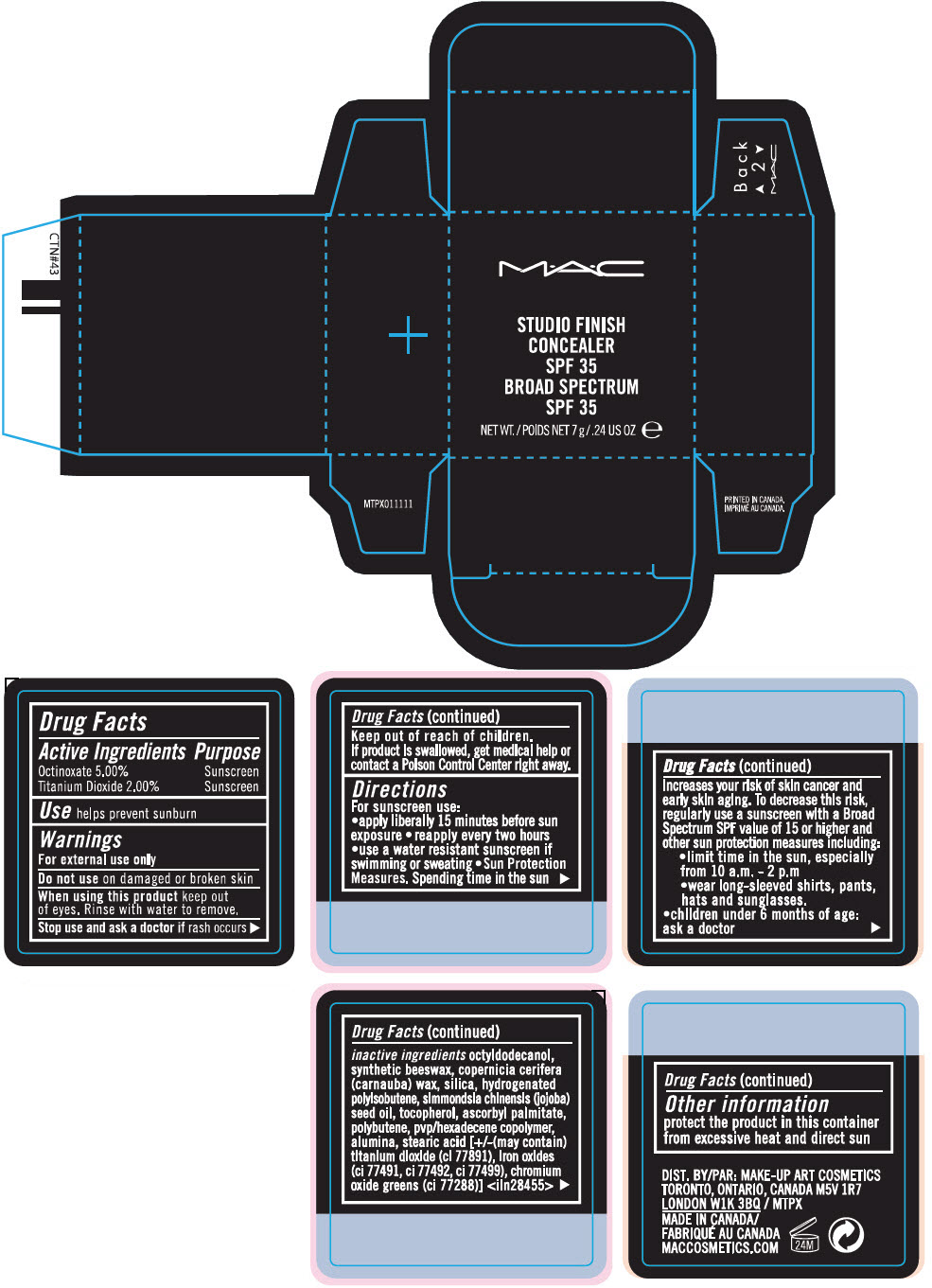 DRUG LABEL: STUDIO FINISH CONCEALER BROAD SPECTRUM SPF 35
NDC: 40046-0078 | Form: PASTE
Manufacturer: MAKEUP ART COSMETICS
Category: otc | Type: HUMAN OTC DRUG LABEL
Date: 20241217

ACTIVE INGREDIENTS: OCTINOXATE 5 g/100 g; TITANIUM DIOXIDE 2 g/100 g
INACTIVE INGREDIENTS: OCTYLDODECANOL; CARNAUBA WAX; SILICON DIOXIDE; HYDROGENATED POLYBUTENE (1300 MW); JOJOBA OIL; TOCOPHEROL; ASCORBYL PALMITATE; POLYBUTENE (1400 MW); ALUMINUM OXIDE; STEARIC ACID; FERRIC OXIDE RED; FERRIC OXIDE YELLOW; FERROSOFERRIC OXIDE; CHROMIC OXIDE

STUDIO FINISH CONCEALER BROAD SPECTRUM SPF 35

Drug Facts

ACTIVE INGREDIENT

Active Ingredients | Purpose
Octinoxate 5.00% | Sunscreen
Titanium Dioxide 2.00% | Sunscreen

Use

helps prevent sunburn

Warnings

For external use only

Do not use on damaged or broken skin

When using this product keep out of eyes. Rinse with water to remove.

Stop use and ask a doctor if rash occurs

Keep out of reach of children.

If product is swallowed, get medical help or contact a Poison Control Center right away.

Directions

For sunscreen use:

- apply liberally 15 minutes before sun exposure
- reapply every two hours
- use a water resistant sunscreen if swimming or sweating
- Sun Protection Measures. Spending time in the sun increases your risk of skin cancer and early skin aging. To decrease this risk, regularly use a sunscreen with a Broad Spectrum SPF value of 15 or higher and other sun protection measures including:
  - limit time in the sun, especially from 10 a.m. - 2 p.m
  - wear long-sleeved shirts, pants, hats and sunglasses.
- children under 6 months of age: ask a doctor

inactive ingredients

octyldodecanol, synthetic beeswax, copernicia cerifera (carnauba) wax, silica, hydrogenated polyisobutene, simmondsia chinensis (jojoba) seed oil, tocopherol, ascorbyl palmitate, polybutene, pvp/hexadecene copolymer, alumina, stearic acid [+/-(may contain) titanium dioxide (ci 77891), iron oxides (ci 77491, ci 77492, ci 77499), chromium oxide greens (ci 77288)] <iln28455>

Other information

protect the product in this container from excessive heat and direct sun

DIST. BY: MAKE-UP ART COSMETICS
TORONTO, ONTARIO, CANADA M5V 1R7

PRINCIPAL DISPLAY PANEL - 7 g Jar Carton

M•A•C

STUDIO FINISH
CONCEALER
SPF 35
BROAD SPECTRUM
SPF 35

NET WT. 7 g/.24 US OZ e